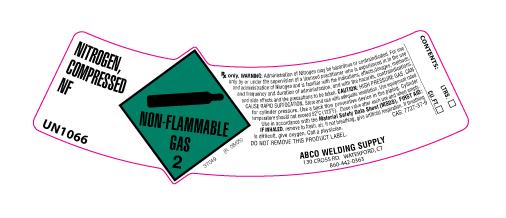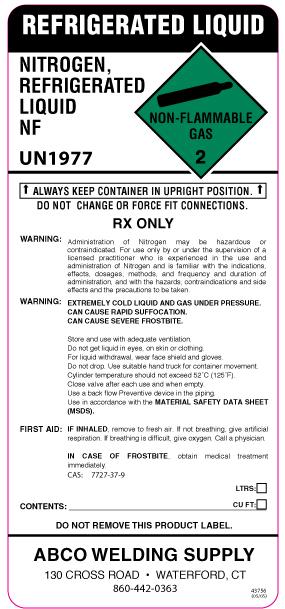 DRUG LABEL: Nitrogen
NDC: 54949-002 | Form: GAS
Manufacturer: ABCO Welding and Industrial Supply Inc
Category: prescription | Type: HUMAN PRESCRIPTION DRUG LABEL
Date: 20100809

ACTIVE INGREDIENTS: Nitrogen 990 mL/1 L

nitrogen

PACKAGE LABEL

NITROGEN, COMPRESSED NF UN1066
NON-FLAMMABLE GAS 2
Rx only. WARNING: Administration of Nitrogen may be hazardous or contraindicated. For use only by or under the supervision of a licensed practitioner who is experienced in the use and administration of Nitrogen and is familiar with the indications, effects, dosages, methods, and frequency and duration of administration, and with the hazards, contraindications, and side effects and the precautions to be taken. CAUTION: HIGH PRESSURE GAS. CAN CAUSE RAPID SUFFOCATION. Store and use with adequate ventilation. Use equipment rated for cylinder pressure. Use a back flow preventive device in the piping. Cylinder temperature should not exceed 52oC (125oF). Close valve after each use and when empty. Use in accordance with the Material Safety Data Sheet (MSDS). FIRST AID: IF INHALED, remove to fresh. air. If not breathing, give artificial respiration. If breathing is difficult, give oxygen. Call a physician.
DO NOT REMOVE THIS PRODUCT LABEL.
CAS:7727-37-9
ABCO WELDING SUPPLY 130 CROSS RD. WATERFORD, CT 860-442-0363
CONTENTS: LTRS. CU. FT.
37049 (R 06/05)

PACKAGE LABEL

REFRIGERATED LIQUID
NITROGEN, REFRIGERATED LIQUID NF UN1977
NON-FLAMMABLE GAS 2
ALWAYS KEEP CONTAINER IN UPRIGHT POSITION. DO NOT CHANGE OR FORCE FIT CONNECTIONS. RX ONLY
WARNING: Administration of Nitrogen may be hazardous or contraindicated. For use only by or under the supervision of a licensed practitioner who is experienced in the use and administration of Nitrogen and is familiar with the indications, effects, dosages, methods, and frequency and duration of administration, and with the hazards, contraindications and side effects and the precautions to be taken.
WARNING: EXTREMELY COLD LIQUID AND GAS UNDER PRESSURE. CAN CAUSE RAPID SUFFOCATION. CAN CAUSE SEVERE FROSTBITE.
Store and use with adequate ventilation.
Do not get liquid in eyes, on skin or clothing.
For liquid withdrawal, wear face shield and gloves.
Do not drop. Use suitable hand truck for container movement.
Cylinder temperature should not exceed 52˚C (125˚F).
Close valve after each use and when empty.
Use a back flow Preventive device in the piping.
Use in accordance with the MATERIAL SAFETY DATA SHEET (MSDS).
FIRST AID:
IF INHALED, remove to fresh air. If not breathing, give artificial respiration. If breathing is difficult, give oxygen. Call a physician.
IN CASE OF FROSTBITE, obtain medical treatment immediately.
DO NOT REMOVE THIS PRODUCT LABEL.
CAS: 7727-37-9
CONTENTS: ____________LTRS: __ CU FT: __
ABCO WELDING SUPPLY 130 CROSS RD WATERFORD, CT 860-442-0363
43756 (05/05)